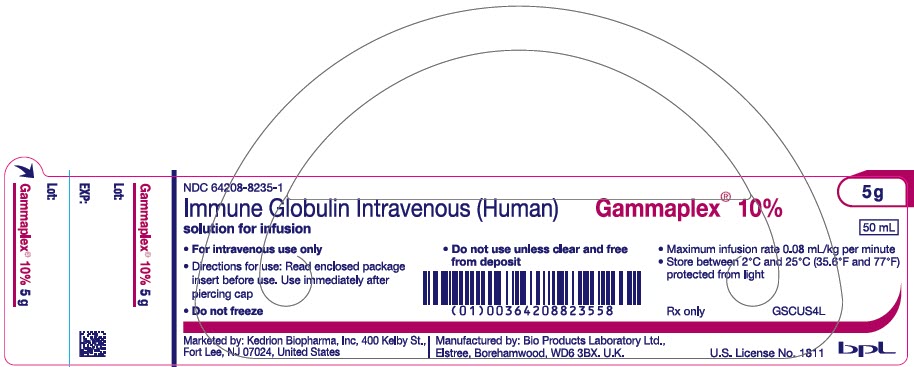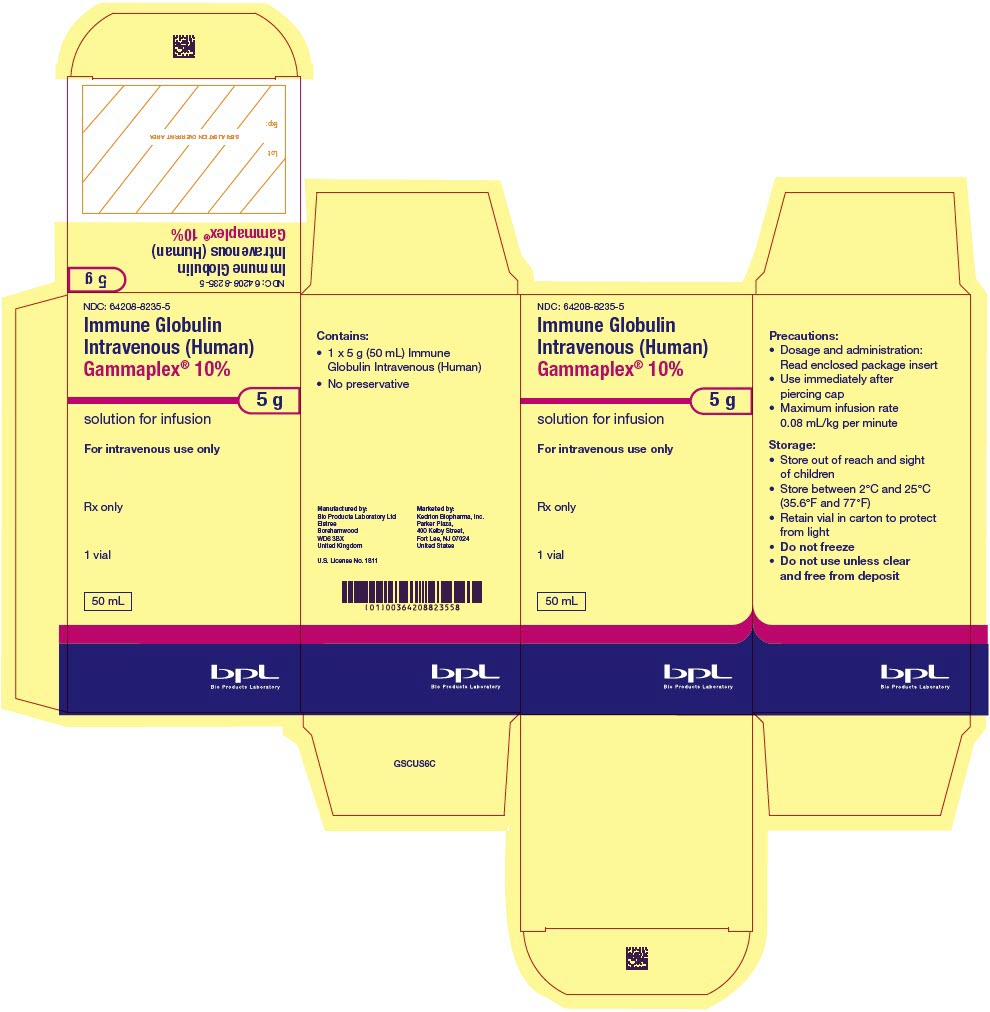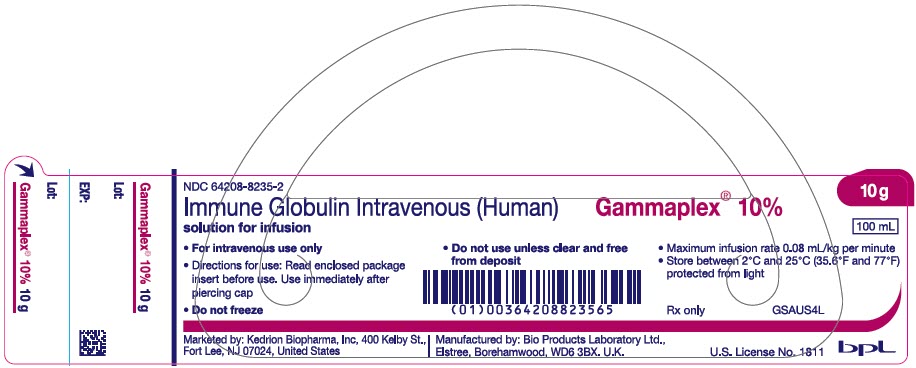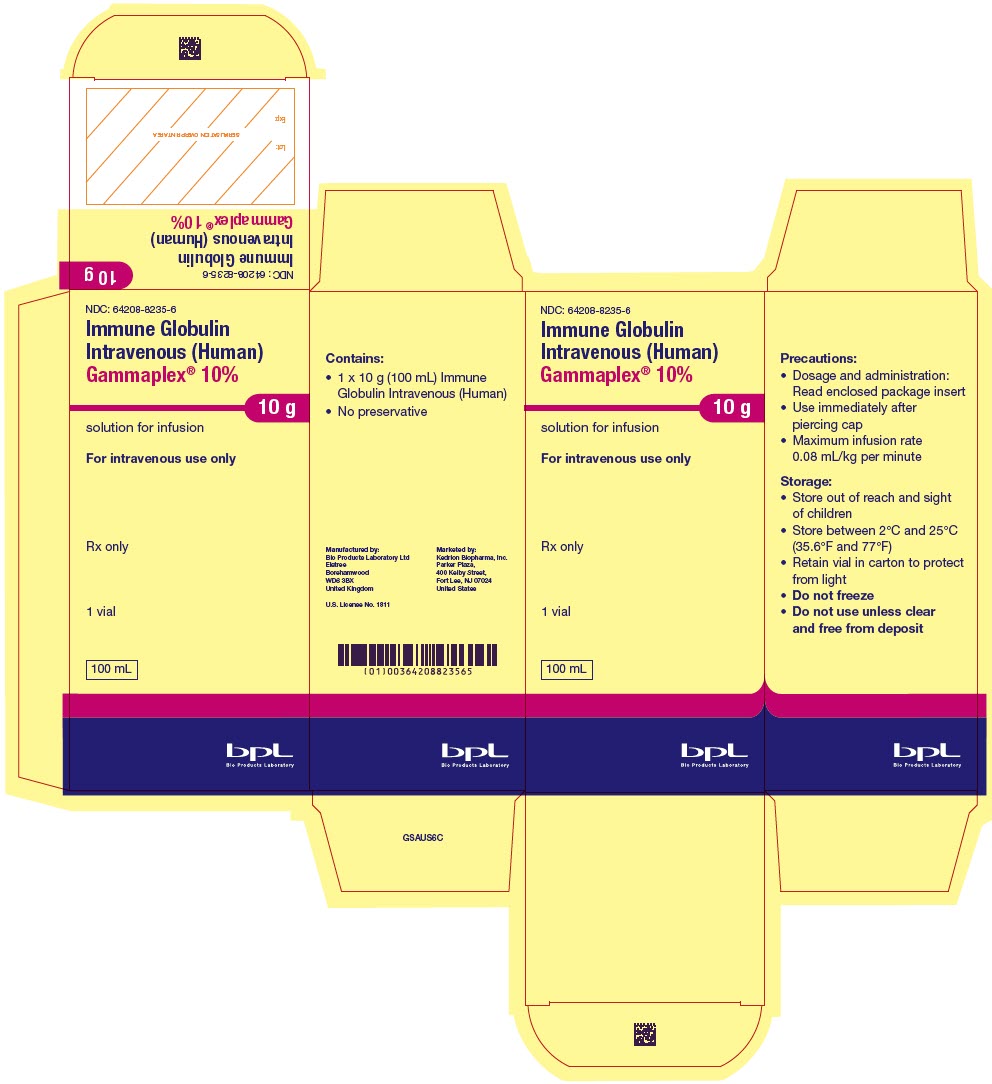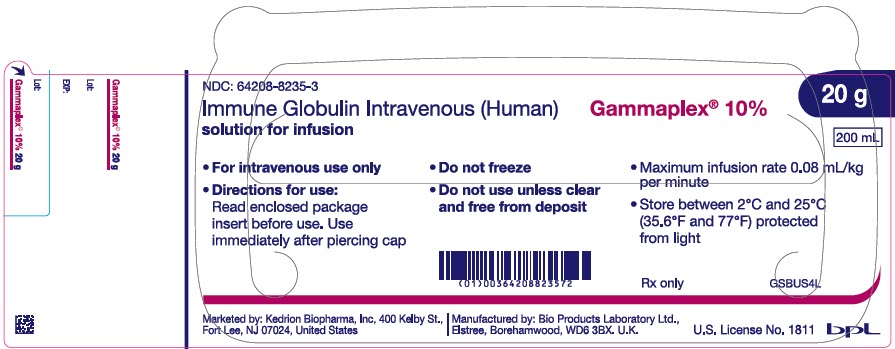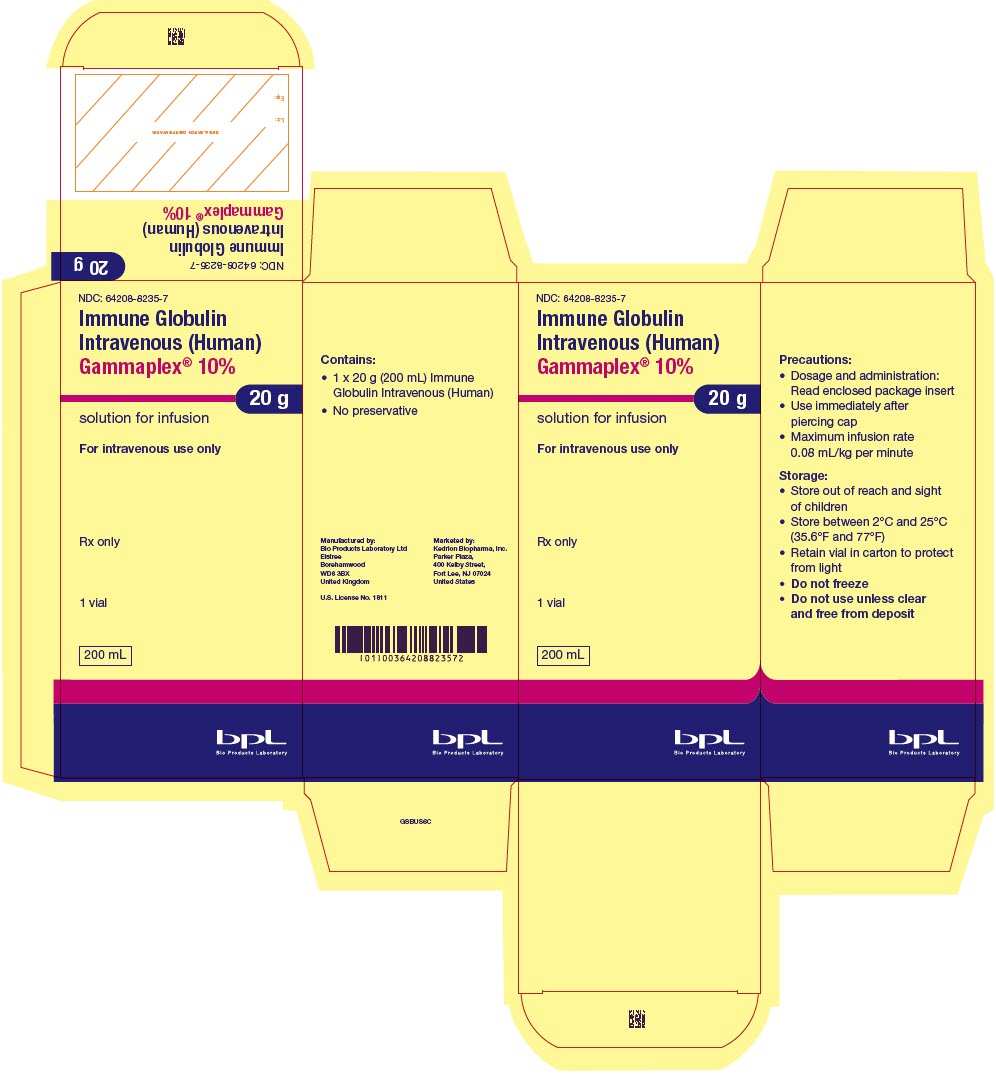 DRUG LABEL: Gammaplex
NDC: 64208-8235 | Form: SOLUTION
Manufacturer: Bio Products Laboratory Ltd
Category: other | Type: PLASMA DERIVATIVE
Date: 20251023

ACTIVE INGREDIENTS: HUMAN IMMUNOGLOBULIN G 5 g/50 mL
INACTIVE INGREDIENTS: GLYCINE 0.9 g/50 mL; POLYSORBATE 80 0.001 g/50 mL; SODIUM CHLORIDE; ACETATE ION

HIGHLIGHTS OF PRESCRIBING INFORMATION

These highlights do not include all the information needed to use GAMMAPLEX® 10% safely and effectively. See full prescribing information for GAMMAPLEX 10%.
GAMMAPLEX 10% Immune Globulin Intravenous [Human], 10% Liquid
Initial U.S. Approval: 2017

WARNING: THROMBOSIS, RENAL DYSFUNCTION and ACUTE RENAL FAILURE

See full prescribing information for complete boxed warning.

- Thrombosis may occur with immune globulin products, including GAMMAPLEX 10%. Risk factors may include: advanced age, prolonged immobilization, hypercoagulable conditions, history of venous or arterial thrombosis, use of estrogens, indwelling vascular catheters, hyperviscosity and cardiovascular risk factors (5.2)
- Renal dysfunction, acute renal failure, osmotic nephrosis, and death^1 may occur in predisposed patients with immune globulin intravenous (lGIV) products, including GAMMAPLEX 10%
- Renal dysfunction and acute renal failure occur more commonly with IGIV products containing sucrose. GAMMAPLEX 10% does not contain sucrose (5.1)
- For patients at risk of thrombosis, renal dysfunction or acute renal failure, administer GAMMAPLEX 10% at the minimum dose and infusion rate practicable. Ensure adequate hydration in patients before administration. Monitor for signs and symptoms of thrombosis and assess blood viscosity in patients at risk for hyperviscosity (2.3, 5.2)

1 INDICATIONS AND USAGE

GAMMAPLEX 10% is an Immune Globulin Intravenous (Human) 10% Liquid indicated for the treatment of:

- primary humoral immunodeficiency (PI) in adults and pediatric patients 2 years of age and older (1.1)
- chronic immune thrombocytopenic purpura (ITP) in adults (1.2)

2 DOSAGE AND ADMINISTRATION

For Intravenous Use Only

Indication | Dose | Initial infusion rate | Maintenance infusion rate (if tolerated)
PI | 300-800 mg/kg (3-8 mL/kg) every 3-4 weeks | 0.5 mg/kg/min (0.005 mL/kg/min) for 15 minutes | Increase gradually every 15 minutes to 8 mg/kg/min (0.08 mL/kg/min)
ITP | 1 g/kg (10 mL/kg) for 2 consecutive days | 0.5 mg/kg/min (0.005 mL/kg/min) for 15 minutes | Increase gradually every 15 minutes to 8 mg/kg/min (0.08 mL/kg/min)

- Ensure that patients with pre-existing renal insufficiency are not volume depleted; discontinue GAMMAPLEX 10% if renal function deteriorates (2.3, 5.1)
- For patients at risk of renal dysfunction, thrombotic events or volume overload, administer GAMMAPLEX 10% at the minimum infusion rate practicable (2.3, 5.1, 5.2, 5.8)

3 DOSAGE FORMS AND STRENGTHS

GAMMAPLEX 10% is a liquid solution containing 10% IgG (100 mg/mL).

4 CONTRAINDICATIONS

- History of anaphylactic or severe systemic reactions to human immunoglobulin (4)
- IgA-deficient patients with antibodies against IgA and a history of hypersensitivity (4)

5 WARNINGS AND PRECAUTIONS

- IgA-deficient patients with antibodies to IgA are at greater risk of developing severe hypersensitivity and anaphylactic reactions (5.3)
- Hyperproteinemia, increased serum viscosity, and hyponatremia may occur in patients receiving IGIV therapy (5.4)
- Aseptic meningitis syndrome may occur, especially with high doses or rapid infusion (5.5)
- Hemolysis, either intravascular or due to enhanced red blood cell sequestration, can develop subsequent to GAMMAPLEX 10% treatments. Risk factors include high doses and non-O blood group. Closely monitor patients for hemolysis and hemolytic anemia (5.6)
- Monitor patients for pulmonary adverse reactions (transfusion-related acute lung injury [TRALI]) (5.7)
- Volume overload can occur. Monitor for signs and symptoms (5.8)
- Consider risks and benefits before prescribing the high dose regimen for chronic ITP in patients at risk of thrombosis, hemolysis, acute kidney injury, or volume overload (5)
- GAMMAPLEX 10% is made from human plasma and may contain infectious agents, e.g. viruses and, theoretically, the Creutzfeldt-Jakob disease agent (5.9)
- Passive transfer of antibodies may confound serologic testing (5.10)

6 ADVERSE REACTIONS

- PI - The most common adverse reactions reported in ≥5% of clinical trial subjects were headache, migraine and pyrexia (6)
- Chronic ITP - The safety of GAMMAPLEX 10% has not been established in patients with ITP. However, the safety of GAMMAPLEX 5% has been studied in subjects with ITP, and it is anticipated that the safety profile for both formulations are comparable for ITP patients. Hence adverse reaction information is presented for GAMMAPLEX 5% where relevant. The most common adverse reactions reported with GAMMAPLEX 5% in ≥5% of clinical trial subjects with ITP were headache, vomiting, pyrexia, nausea, arthralgia and dehydration (6)

To report SUSPECTED ADVERSE REACTIONS, contact Kedrion Biopharma Inc. at 1-855-3KDRION (1-855-353-7466) or the FDA at 1-800-FDA-1088 or www.fda.gov/medwatch

7 DRUG INTERACTIONS

- Passive transfer of antibodies may transiently interfere with the immune response to live virus vaccines, e.g. measles, mumps, and rubella (7)
- Therapy with GAMMAPLEX 10% may confound serological testing (7)

8 USE IN SPECIFIC POPULATIONS

- Pediatrics: In pediatric patients 2 years of age and older, the pharmacokinetics, dosage and safety are similar to those in adults (8.4)
- Geriatrics: In patients over the age of 65 years or in any patient at risk of developing renal insufficiency, do not exceed the recommended dose and infuse GAMMAPLEX 10% at the minimum rate practicable (8.5)

FULL PRESCRIBING INFORMATION

WARNING: THROMBOSIS, RENAL DYSFUNCTION and ACUTE RENAL FAILURE

- Thrombosis may occur with immune globulin products, including GAMMAPLEX 10%. Risk factors may include: advanced age, prolonged immobilization, hypercoagulable conditions, history of venous or arterial thrombosis, use of estrogens, indwelling central vascular catheters, hyperviscosity and cardiovascular risk factors. Thrombosis may occur in the absence of known risk factors [see Warnings and Precautions (5.2), Patient Counseling Information (17)].
- Renal dysfunction, acute renal failure, osmotic nephrosis, and death^1 may occur in predisposed patients who receive immune globulin intravenous (lGIV) products.
- Patients predisposed to renal dysfunction include those with any degree of pre-existing renal insufficiency, diabetes mellitus, age greater than 65 years, volume depletion, sepsis, paraproteinemia, or patients receiving known nephrotoxic drugs [see Warnings and Precautions (5.1)]. Renal dysfunction and acute renal failure occur more commonly in patients receiving IGIV products containing sucrose. GAMMAPLEX 10% does not contain sucrose.
- For patients at risk of thrombosis, renal dysfunction or acute renal failure, administer GAMMAPLEX 10% at the minimum dose and infusion rate practicable. Ensure adequate hydration in patients before administration. Monitor for signs and symptoms of thrombosis and assess blood viscosity in patients at risk for hyperviscosity [see Dosage and Administration (2.1, 2.3), Warnings and Precautions (5.2)].

1 INDICATIONS AND USAGE

1.1 Primary Humoral Immunodeficiency (PI)

GAMMAPLEX 10% is an Immune Globulin Intravenous (Human), 10% Liquid indicated for replacement therapy in primary humoral immunodeficiency (PI) in adults and pediatric patients 2 years of age and older. This includes, but is not limited to, the humoral immune defect in common variable immunodeficiency, X-linked agammaglobulinemia, congenital agammaglobulinemia, Wiskott-Aldrich syndrome, and severe combined immunodeficiencies.

1.2 Chronic Immune Thrombocytopenic Purpura (ITP)

GAMMAPLEX 10% is indicated for the treatment of chronic immune thrombocytopenic purpura (ITP) in adults to raise platelet counts.

2 DOSAGE AND ADMINISTRATION

For Intravenous Use Only

2.1 Dosage

Table 1: Recommended Dosage and Administration for GAMMAPLEX 10%
Indication | Dose | Initial infusion rate | Maintenance infusion rate (if tolerated)
PI | 300-800 mg/kg (3-8 mL/kg) every 3-4 weeks | 0.5 mg/kg/min (0.005 mL/kg/min) for 15 minutes | Increase gradually every 15 minutes to 8 mg/kg/min (0.08 mL/kg/min)
ITP | 1 g/kg (10 mL/kg) for 2 consecutive days | 0.5 mg/kg/min (0.005 mL/kg/min) for 15 minutes | Increase gradually every 15 minutes to 8 mg/kg/min (0.08 mL/kg/min)

Treatment of Primary Humoral Immunodeficiency

As there are significant differences in the half-life of IgG among patients with PI, the frequency and amount of immunoglobulin therapy may vary from patient to patient. The proper amount can be determined by monitoring clinical response.

The recommended dose of GAMMAPLEX 10% for patients with PI is 300 to 800 mg/kg (3 to 8 mL/kg), administered every 3 to 4 weeks. If a patient has been exposed to measles, it may be prudent to administer an extra dose of Immune Globulin Intravenous as soon as possible and within 6 days of exposure. A dose of 400 mg/kg should provide a serum level > 240 mIU/mL of measles antibodies for at least two weeks. If a patient is at risk of future measles exposure and receives a dose of less than 530 mg/kg every 3-4 weeks, the dose should be increased to at least 530 mg/kg. This should provide a serum level of 240 mIU/mL of measles antibodies for at least 22 days after infusion. Adjust the dosage over time to achieve the desired serum trough levels and clinical response. If a patient misses a dose, administer the missed dose as soon as possible, and then resume scheduled treatments every 3 or 4 weeks, as applicable.

Treatment of Chronic Immune Thrombocytopenic Purpura

The recommended dose of GAMMAPLEX 10% for patients with ITP is 1 g/kg (10 mL/kg) on 2 consecutive days, providing a total dose of 2 g/kg. Carefully consider the relative risks and benefits before prescribing the high dose regimen (i.e. 1 g/kg/day for 2 days) in patients at increased risk of thrombosis, hemolysis, acute kidney injury, or volume overload [see Warnings and Precautions (5)]. Adequate data on the platelet response to the low dose regimen (e.g. 400 mg/kg per day for 5 consecutive days) are not available for GAMMAPLEX 10%.

2.2 Preparation and Handling

- GAMMAPLEX 10% is a clear or slightly opalescent, colorless or pale yellow liquid. Visually inspect parenteral drug products for particulate matter and discoloration prior to administration whenever solution and container permit. Do not use if the solution is cloudy or turbid, or if it contains particulate matter
- GAMMAPLEX 10% vials are for single use only. Dispose of partially used or unused product
- GAMMAPLEX 10% contains no antimicrobial preservatives. Therefore, prompt administration after preparation is necessary
- Do not shake
- Administer GAMMAPLEX 10% at room temperature (up to 25°C [77°F])
- Do not use any solution that has been frozen [see How Supplied/ Storage and Handling (16)]
- Infuse GAMMAPLEX 10% using a separate infusion line
- Do not mix GAMMAPLEX 10% with other intravenous medications (including normal saline) or other IGIV products
- An infusion pump may be used to control the rate of administration
- For administration of large doses, pool multiple vials using aseptic technique

2.3 Administration

- Hydrate the patient adequately prior to the initiation of infusion
- Infuse GAMMAPLEX 10% intravenously using an intravenous infusion set. See Table 1 for recommended infusion rates
- Monitor vital signs throughout the infusion
- Slow or stop the infusion if adverse reactions occur
- If symptoms subside, the infusion may be resumed at a lower rate that is comfortable for the patient
- The observation time of patients after GAMMAPLEX 10% administration may vary. If the patient (a) has not received GAMMAPLEX 10% or another IgG product, (b) is switched from an alternative IGIV product or (c) has had a long interval since the previous infusion, prolong the observation time for adverse reactions after GAMMAPLEX 10% infusion
- Certain severe adverse reactions may be related to the rate of infusion. Slowing or stopping the infusion often allows the reaction to disappear
- Close monitoring of the infusion rate in pediatric patients is recommended
- Ensure that patients with pre-existing renal insufficiency are not volume depleted
- For patients at increased risk of renal dysfunction, thrombotic events, or volume overload, administer GAMMAPLEX 10% at the minimum infusion rate practicable. Consider discontinuing GAMMAPLEX 10% administration if renal function deteriorates [see Boxed Warning, Warnings and Precautions (5.1, 5.2, 5.8)]

3 DOSAGE FORMS AND STRENGTHS

GAMMAPLEX 10% is a liquid solution containing 10% IgG (100 mg/mL).

4 CONTRAINDICATIONS

- GAMMAPLEX 10% is contraindicated in patients who have had an anaphylactic or severe systemic reaction to the administration of human immune globulin
- GAMMAPLEX 10% is contraindicated in IgA-deficient patients with antibodies to IgA and a history of hypersensitivity

5 WARNINGS AND PRECAUTIONS

5.1 Renal Dysfunction/Failure

Acute renal dysfunction/failure, osmotic nephropathy, and death^1 may occur upon use of human IGIV products. Ensure that patients are not volume depleted before administering GAMMAPLEX 10%. In patients who are at risk of developing renal dysfunction, because of pre-existing renal insufficiency, predisposition to acute renal failure (such as diabetes mellitus, hypovolemia, overweight, use of concomitant nephrotoxic medicinal products or age >65 years), administer GAMMAPLEX 10% at the minimum infusion rate practicable [see Dosage and Administration (2.3)].

Periodic monitoring of renal function and urine output is particularly important in patients judged to be at increased risk of developing acute renal failure. Assess renal function, including measurement of blood urea nitrogen (BUN) and serum creatinine, before the initial infusion of GAMMAPLEX 10% and at appropriate intervals thereafter. If renal function deteriorates, consider discontinuing GAMMAPLEX 10%.

5.2 Thrombotic Events

Thrombosis may occur following treatment with immune globulin products, including GAMMAPLEX 10%^2. Risk factors may include: advanced age, prolonged immobilization, hypercoagulable conditions, history of venous or arterial thrombosis, use of estrogens, indwelling central vascular catheters, hyperviscosity and cardiovascular risk factors. Thrombosis may occur in the absence of known risk factors.

Consider baseline assessment of blood viscosity in patients at risk for hyperviscosity, including those with cryoglobulins, fasting chylomicronemia/markedly high triacylglycerols (triglycerides), or monoclonal gammopathies. For patients at risk of thrombosis, administer GAMMAPLEX 10% at the minimum dose and infusion rate practicable. Ensure adequate hydration in patients before administration. Monitor for signs and symptoms of thrombosis and assess blood viscosity in patients at risk for hyperviscosity [see Boxed Warning, Dosage and Administration (2.3), Patient Counseling Information (17)].

5.3 Hypersensitivity

Severe hypersensitivity reactions may occur [see Contraindications (4)]. In case of hypersensitivity, discontinue GAMMAPLEX 10% infusion immediately and institute appropriate treatment. Medications such as epinephrine should be available for immediate treatment of acute hypersensitivity reactions.

GAMMAPLEX 10% contains trace amounts of IgA (<20 micrograms/mL) [see Description (11)]. Patients with known antibodies to IgA may have a greater risk of developing potentially severe hypersensitivity and anaphylactic reactions. GAMMAPLEX 10% is contraindicated in patients with antibodies against IgA and a history of hypersensitivity reaction [see Contraindications (4)].

5.4 Hyperproteinemia, Increased Serum Viscosity, and Hyponatremia

Hyperproteinemia, increased serum viscosity, and hyponatremia may occur in patients receiving IGIV therapy. It is critical to clinically distinguish true hyponatremia from a pseudohyponatremia that is associated with or causally related to hyperproteinemia with concomitant decreased calculated serum osmolality or elevated osmolar gap, because treatment aimed at decreasing serum free water in patients with pseudohyponatremia may lead to volume depletion, a further increase in serum viscosity, and a possible predisposition to thrombotic events^2.

5.5 Aseptic Meningitis Syndrome (AMS)

AMS may occur with IGIV treatment. AMS usually begins within several hours to 2 days following IGIV treatment. Discontinuation of IGIV treatment has resulted in remission of AMS within several days without sequelae^3.

AMS is characterized by the following signs and symptoms: severe headache, nuchal rigidity, drowsiness, fever, photophobia, painful eye movements, nausea, and vomiting [see Patient Counseling Information (17)]. Cerebrospinal fluid (CSF) studies frequently reveal pleocytosis up to several thousand cells per cubic millimeter, predominantly from the granulocytic series, and elevated protein levels up to several hundred mg/dL, but negative culture results. Conduct a thorough neurological examination on patients exhibiting such signs and symptoms, including CSF studies, to rule out other causes of meningitis. AMS may occur more frequently in association with high doses (2 g/kg) and/or rapid infusion of IGIV.

5.6 Hemolysis

GAMMAPLEX 10% may contain blood group antibodies that can act as hemolysins and induce in vivo coating of red blood cells (RBCs) with immunoglobulin, causing a positive direct antiglobulin test (DAT) (Coombs' test) result and hemolysis^4. Delayed hemolytic anemia can develop subsequent to IGIV therapy due to enhanced RBC sequestration; acute hemolysis, consistent with intravascular hemolysis, has been reported^5. Cases of severe hemolysis-related renal dysfunction/failure or disseminated intravascular coagulation have occurred following infusion of IGIV.

The following risk factors may be associated with the development of hemolysis following IGIV administration: high doses (e.g. ≥2 g/kg), given either as a single administration or divided over several days, and non-O blood group^6. Other individual patient factors, such as an underlying inflammatory state (as may be reflected by, for example, elevated C-reactive protein or erythrocyte sedimentation rate), have been hypothesized to increase the risk of hemolysis following administration of IGIV^7, but their role is uncertain. Hemolysis has been reported following administration of IGIV for a variety of indications, including ITP and PI^4.

Closely monitor patients for clinical signs and symptoms of hemolysis, particularly patients with risk factors noted above. Consider appropriate laboratory testing in higher risk patients, including measurement of hemoglobin or hematocrit prior to infusion and within approximately 36 to 96 hours post infusion. If clinical signs and symptoms of hemolysis or a significant drop in hemoglobin or hematocrit have been observed, perform confirmatory laboratory testing. If transfusion is indicated for patients who develop hemolysis with clinically compromising anemia after receiving IGIV, perform adequate cross-matching to avoid exacerbating on-going hemolysis.

5.7 Transfusion-related Acute Lung Injury (TRALI)

Noncardiogenic pulmonary edema may occur in patients following IGIV treatment^8. TRALI is characterized by severe respiratory distress, pulmonary edema, hypoxemia, normal left ventricular function and fever. Symptoms typically appear within 1 to 6 hours following treatment.

Monitor patients for pulmonary adverse reactions. If TRALI is suspected, perform appropriate tests for the presence of anti-neutrophil antibodies in both the product and the patient's serum.

TRALI may be managed using oxygen therapy with adequate ventilatory support.

5.8 Volume Overload

Carefully consider the relative risks and benefits before prescribing the high dose regimen (for chronic ITP) in patients at increased risk of volume overload.

5.9 Transmissible Infectious Agents

As GAMMAPLEX 10% is made from human blood, it may carry a risk of transmitting infectious agents, e.g. viruses, the variant Creutzfeldt-Jakob disease (vCJD) agent and, theoretically, the Creutzfeldt-Jakob disease (CJD) agent. No cases of transmission of viral diseases or CJD have been associated with the use of GAMMAPLEX 10%. All infections suspected by a physician possibly to have been transmitted by this product should be reported by the physician or other healthcare providers to Kedrion Biopharma, Inc. at 1-855-3KDRION (1-855-353-7466)

Before prescribing GAMMAPLEX 10%, the physician should discuss the risks and benefits of its use with the patient [see Patient Counseling Information (17)].

5.10 Laboratory Tests

- After infusion of immunoglobulin, the transitory rise of the various passively transferred antibodies in the patient's blood may yield positive serological testing results, with the potential for misleading interpretation
- Passive transmission of antibodies to erythrocyte antigens (e.g. A, B, and D) may cause a positive direct or indirect antiglobulin (Coombs') test
- Clinically assess patients with known renal dysfunction, diabetes mellitus, age greater than 65 years, volume depletion, sepsis, paraproteinemia, or those receiving nephrotoxic agents, and monitor as appropriate (BUN, serum creatinine, urine output) during therapy with GAMMAPLEX 10%
- Consider baseline assessment of blood viscosity in patients at risk for hyperviscosity, including those with polycythemia, cryoglobulins, fasting chylomicronemia/markedly high triglycerides, or monoclonal gammopathies
- Consider measuring hemoglobin or hematocrit at baseline and approximately 36 to 96 hours post infusion in patients at higher risk of hemolysis. If signs and/or symptoms of hemolysis are present after an infusion of GAMMAPLEX 10%, perform appropriate laboratory testing for confirmation
- If TRALI is suspected, perform appropriate tests for the presence of anti-neutrophil antibodies in both the product and patient's serum

6 ADVERSE REACTIONS

The safety information for GAMMAPLEX 10% is based on the clinical trial evaluating the bioequivalence of GAMMAPLEX 10% to GAMMAPLEX 5% in subjects with PI. The safety of GAMMAPLEX 10% has not been established in patients with ITP. However, the safety profile for GAMMAPLEX 5% has been studied in subjects with ITP, and it is anticipated that the safety profile for both formulations are comparable for ITP patients. Hence adverse reaction (AR) information is presented for GAMMAPLEX 5% where relevant. ARs are adverse events that were deemed by the investigators as causally related to GAMMAPLEX 10%.

There were no serious ARs observed with GAMMAPLEX 10% in the clinical trial in adult or pediatric subjects with PI.

Serious ARs observed with GAMMAPLEX 5% in clinical trial subjects with ITP were headache, vomiting and dehydration. In addition, following a review of the data, 4 subjects (11%) were considered to have experienced asymptomatic suspected treatment-emergent hemolysis [see Clinical Trials Experience (6.1)].

The following potential serious ARs are described above and/or elsewhere in the labeling:

- Thrombotic Events [see Warnings and Precautions (5.2)]
- Hemolysis [see Warnings and Precautions (5.6)]

The most common ARs occurring in ≥5% of adult subjects receiving GAMMAPLEX 10% in the PI clinical trial were headache (4 subjects, 12.5%), migraine (2 subjects, 6.3%) and pyrexia (2 subjects, 6.3%) and for pediatric subjects 3 years of age and older, in the same study, headache (3 subjects, 20.0%); other ARs occurred in a single pediatric subject. Overall, ARs which occurred in ≥5% of the adult and pediatric subjects combined are shown in Table 2.

The most common ARs occurring in ≥5% of adult subjects receiving GAMMAPLEX 5% in the chronic ITP clinical trial were headache (10 subjects, 28.6%), vomiting (6 subjects, 17.1%), pyrexia (5 subjects, 14.3%), nausea (3 subjects, 8.6%), arthralgia (2 subjects, 5.7%) and dehydration (2 subjects, 5.7%).

6.1 Clinical Trials Experience

Because clinical trials are conducted under widely varying conditions, adverse reaction rates observed in the clinical trials of a drug cannot be directly compared to rates in the clinical trials of another drug and may not reflect the rates observed in clinical practice.

Primary Humoral Immunodeficiency Study

A multicenter, open-label, randomized two-period crossover study (bioequivalence study) evaluated the PK, safety and tolerability of GAMMAPLEX 10% and GAMMAPLEX 5% in 33 adults aged 17 to 55 years with PI. Twenty one (63.6%) subjects were female and 12 (36.4%) were male; 33 (100%) were White, of which 1 (3.0%) was Hispanic or Latino. The safety analysis included all 33 subjects for GAMMAPLEX 5% and 32 subjects for GAMMAPLEX 10%. One subject withdrew consent during the first infusion of GAMMAPLEX 5%, citing inconvenience of the study visits. Thirty two subjects received at least five infusions of each product either on a 28-day or 21-day cycle. The mean doses per infusion for GAMMAPLEX 10% were 491.7 mg/kg and 499 mg/kg respectively, and were similar for GAMMAPLEX 5% [see Clinical Studies (14.1)]. No subjects were on regular systemic corticosteroids at entry to, or during the study. Twelve (36.4%) adult subjects received short courses of corticosteroids, from a single dose to a maximum of 6 days duration, for various clinical conditions. No subjects received corticosteroids as premedications for GAMMAPLEX infusions. The use of local anesthetics, antipyretics, antihistamines, analgesics, and antiemetics before infusion was allowed; three (9.1%) adult subjects received a total of 5 courses of such premedication.

While on GAMMAPLEX 10%, 10 of the adults (31.3%) had an adverse reaction (AR) with a similar proportion (12; 36.4%) when on GAMMAPLEX 5%. Headache was the most commonly reported AR with both formulations of GAMMAPLEX. In total, 166 infusions of GAMMAPLEX 10% and 163 infusions of GAMMAPLEX 5% were given to adults during the study.

Two subjects had a positive direct antiglobulin (Coombs') test (DAT; DCT) result at some stage in the study. For one adult, the test was positive before starting in the study and it remained positive throughout, but without evidence of hemolysis. One other adult had a positive DAT one week after an infusion of GAMMAPLEX 5% but there was no evidence of hemolysis and no positive DAT results when receiving GAMMAPLEX 10%. No other adults had a positive DAT during the study.

In the same study, 15 pediatric subjects with PI, 3 years of age and older, received GAMMAPLEX 10%. All subjects were White, of which 2 (13.3%) were Hispanic or Latino. The mean doses per infusion were 552.9 mg/kg for subjects on the 28-day cycle (n=8) and 514.7 mg/kg for subjects on the 21-day cycle (n=7), overall range 343 to 745 mg/kg. Two subjects were in the 2-5 year age group, 7 were in the 6-11 year age group and 6 were in the 12-15 year age group. Fourteen subjects completed the study with at least 5 infusions of GAMMAPLEX 10% (pediatric subjects only received GAMMAPLEX 10% in this study); 82 infusions were given in total. Two pediatric subjects received IV methylprednisolone as premedication for each infusion. Local anesthetics, antipyretics, antihistamines and analgesics were allowed.

While on GAMMAPLEX 10%, 6 (40%) pediatric subjects had an AR. Headache was the most common with 3 subjects (20%) reporting a total of 4 events. All other ARs were not reported by more than a single pediatric subject. One pediatric subject had a positive direct antiglobulin (Coombs') test without evidence of hemolysis.

Table 2 lists the ARs occurring in at least 5% of all subjects (adult and pediatric combined) with PI treated with GAMMAPLEX 10% in the clinical study.

Table 2: Adverse Reactions (ARs [Adverse Reactions (ARs) are defined as adverse events considered by the investigators to have been possibly, probably, or definitely related to administration of GAMMAPLEX.]) Occurring in ≥5% of Subjects with PI Receiving GAMMAPLEX 10% (Adult and Pediatric Subjects Combined)
Preferred Term | Subjects (%) [n=32] | Events
Headache | 7 (14.9) | 16
Migraine | 3 (6.4) | 3
Pyrexia | 3 (6.4) | 3

Chronic Immune Thrombocytopenic Purpura Study

The safety of GAMMAPLEX 10% has not been established in patients with ITP. However, the safety profile for GAMMAPLEX 5% has been studied in subjects with ITP, and it is anticipated that the safety profile for both formulations are comparable for ITP patients. The following is a summary of the study of GAMMAPLEX 5% in chronic ITP. In a multicenter, open-label, non-randomized clinical trial, 35 subjects with chronic ITP were treated with a nominal dose of 1000 mg/kg on each of two consecutive days (total dose 2000 mg/kg). Doses of GAMMAPLEX 5% ranged from 482 to 1149 mg/kg on an infusion day. The median total dose per subject was 2035 mg/kg. Pre-medication with antihistamine or analgesic drugs was permitted if required, but corticosteroids were not permitted prior to infusion as pre-medication. Ten subjects received corticosteroids for ITP during the trial and one additional subject received corticosteroids as pre-medication in violation of the protocol. All 35 subjects received at least one infusion of clinical trial drug, and all but one subject completed the first course of treatment.

Fifteen subjects (42.9%) reported at least one AR (63 in total); the most commonly reported being headache (10 subjects, 28.6%), vomiting (6 subjects, 17.1%), pyrexia (5 subjects, 14.3%), nausea (3 subjects, 8.6%), arthralgia (2 subjects, 5.7%) and dehydration (2 subjects, 5.7%). Three subjects experienced a total of five serious ARs. Of the five serious ARs, one subject had three concurrently (vomiting, dehydration and headache) and two subjects each had one serious AR (headache). One of these latter two subjects discontinued from the clinical trial because of the severe headache. Table 3 lists the ARs in more than ≥5% of subjects. Based on a review of clinical and laboratory data, 4/35 subjects (11%) with drops in hemoglobin exceeding 2 g/dL following administration of GAMMAPLEX 5% were considered to have experienced suspected treatment-emergent hemolysis. Milder treatment-emergent hemolysis could not be excluded for an additional 7 subjects, giving a total of 11 of 35 subjects (31%) for whom hemolysis could not be excluded (not including an additional two subjects who lacked follow-up testing for hemolysis, so their hemolysis status was considered unassessable). Data for two subjects were consistent with possible intravascular hemolysis, including one subject who may also have had an element of extravascular hemolysis. Nine of the possible hemolysis cases were mild and appeared consistent with possible extravascular hemolysis.

There was no evidence of transmission of HBV, HCV, HIV and parvovirus B19 during this clinical trial.

Table 3: Adverse Reactions (ARs [Adverse Reactions (ARs) are defined as adverse events considered by the investigators to have been possibly, probably, or definitely related to administration of GAMMAPLEX.]) Occurring in ≥5% of Subjects with ITP
Adverse Reactions | Subjects (%) [n=35] | Events
Headache | 10 (28.6) | 19
Vomiting | 6 (17.1) | 8
Pyrexia | 5 (14.3) | 6
Nausea | 3 (8.6) | 3
Arthralgia | 2 (5.7) | 3
Dehydration | 2 (5.7) | 2

6.2 Postmarketing Experience

Because adverse reactions are voluntarily reported post-approval from a population of uncertain size, it is not always possible to reliably estimate their frequency or establish a causal relationship to product exposure.

GAMMAPLEX 10% Postmarketing Experience

The following adverse reactions have been identified and reported during the postmarketing use of GAMMAPLEX 10%:

- Cardiovascular: Tachycardia, Thromboembolism, Hypertension, Flushing
- Gastrointestinal: Nausea
- General/Body as a Whole: Chills, Chest discomfort, Pyrexia
- Musculoskeletal: Back pain, Polymyositis
- Neurological: Headache
- Respiratory: Dyspnea
- Integumentary: Rash, Urticaria
- Investigations: Blood Pressure increased, Blood Pressure diastolic decreased

The following adverse reactions have been identified during postmarketing use of intravenous immune globulins^9:

- Infusion reactions: Hypersensitivity (e.g. anaphylaxis), headache, diarrhea, tachycardia, fever, fatigue, dizziness, malaise, chills, flushing, urticaria or other skin reactions, wheezing or other chest discomfort, nausea, vomiting, rigors, back pain, myalgia, arthralgia, and changes in blood pressure
- Renal: Acute renal dysfunction/failure, osmotic nephropathy
- Respiratory: Apnea, Acute Respiratory Distress Syndrome (ARDS), TRALI, cyanosis, hypoxemia, pulmonary edema, dyspnea, bronchospasm, pulmonary embolism
- Cardiovascular: Cardiac arrest, thromboembolism, vascular collapse, hypotension, myocardial infarction
- Neurological: Coma, loss of consciousness, seizures, tremor, aseptic meningitis syndrome, migraine
- Integumentary: Stevens-Johnson syndrome, epidermolysis, erythema multiforme, dermatitis (e.g. bullous dermatitis)
- Hematologic: Pancytopenia, leukopenia, hemolysis, positive direct antiglobulin (Coombs') test
- Musculoskeletal: Musculoskeletal pain
- Gastrointestinal: Hepatic dysfunction, abdominal pain
- General/Body as a Whole: Pyrexia, rigors

7 DRUG INTERACTIONS

- Transitory rise of the various passively transferred antibodies in the patient's blood after infusion of immunoglobulin may yield positive serological testing results, with the potential for misleading interpretation. Passive transmission of antibodies to erythrocyte antigens (e.g. A, B, and D) may cause a positive direct or indirect antiglobulin (Coombs') test.
- Passive transfer of antibodies may transiently interfere with the immune response to live virus vaccines such as measles, mumps, rubella and varicella.^(10, 11)
  Inform the immunizing physician of recent therapy with GAMMAPLEX 10% so that appropriate measures may be taken [see Patient Counseling Information (17)].

8 USE IN SPECIFIC POPULATIONS

8.1 Pregnancy

Risk Summary

Animal reproduction studies have not been conducted with GAMMAPLEX 10%. It is also not known whether GAMMAPLEX 10% can cause fetal harm when administered to a pregnant woman or can affect reproduction capacity. GAMMAPLEX 10% should be given to a pregnant woman only if clearly needed. Immunoglobulins cross the placenta from maternal circulation increasingly after 30 weeks of gestation.^12

8.2 Lactation

Risk Summary

Use of GAMMAPLEX 10% has not been evaluated in breast-feeding mothers.

8.4 Pediatric Use

In pediatric subjects 3 years of age and older, the pharmacokinetics, dosage and safety are similar to those in adults.

Treatment of Primary Humoral Immunodeficiency

GAMMAPLEX 10% was evaluated in 13 pediatric patients with primary humoral immunodeficiency (2 between ages of 3 to 5, 6 between ages of 6 to 11, and 5 between ages of 12 to 15). No pediatric-specific dose requirements were necessary to achieve the desired serum IgG levels [see Clinical Studies (14)]. The safety and pharmacokinetics of GAMMAPLEX 10% were assessed in pediatric subjects 3 years of age and older with PI [see Clinical Studies (14)].

Treatment of Chronic Immune Thrombocytopenic Purpura

The safety and effectiveness of GAMMAPLEX 10% has not been established in pediatric patients with ITP. GAMMAPLEX 5% was evaluated in three (3) pediatric subjects with chronic ITP (two aged 6 years and one aged 12 years). This number of pediatric patients was too small for separate evaluation from the adult patients for efficacy [see Clinical Studies (14)].

8.5 Geriatric Use

Use caution when administering GAMMAPLEX 10% to patients aged 65 years and over who are judged to be at increased risk of developing renal insufficiency or thrombotic events [see Boxed Warning, Warnings and Precautions (5.1, 5.2)]. Do not exceed recommended doses, and administer GAMMAPLEX 10% at the minimum infusion rate practicable.

No subjects over the age of 55 years were included in the clinical study of GAMMAPLEX 10%. Eight (8) patients with PI at or over the age of 65 years were included within the clinical evaluation of GAMMAPLEX 5%. The number of geriatric patients was too small for separate evaluation from the younger patients for safety or efficacy [see Clinical Studies (14)].

10 OVERDOSAGE

Overdosage may lead to fluid overload and hyperviscosity, particularly in the elderly and in patients with renal impairment.

11 DESCRIPTION

GAMMAPLEX 10% is a ready to use sterile solution of polyclonal human Immunoglobulin G for intravenous administration that contains glycine and polysorbate 80 as stabilizers. Specifically, GAMMAPLEX 10% contains approximately 10 g normal human immunoglobulin and 200-300 mM glycine in 100 mL of buffer solution containing: <30 mM acetate, <30 mM sodium chloride and 1-6 mg polysorbate 80. Immunoglobulin G purity is ≥98%, the pH is in the range of 4.9 to 5.3, and osmolality is not less than 240 mOsmol/kg (typically 280 mOsmol/kg). The distribution of the four IgG subclasses reflects that of normal plasma. The content of IgA is less than 20 micrograms/mL. The anti-D and anti-A/anti-B hemagglutinin content of the drug product is strictly controlled to specification.

GAMMAPLEX 10% contains no reducing carbohydrate stabilizers (e.g. sucrose, maltose) and no preservative.

GAMMAPLEX 10% is prepared from large pools of human plasma by a combination of cold ethanol fractionation and ion exchange chromatography. Fab functions tested include antigen binding activity, and Fc functions tested include complement activation and rubella antibody-mediated hemolysis.

GAMMAPLEX 10% is manufactured from plasma, obtained from healthy US donors, who have passed viral screening tests. All donors are subjected to medical examinations, laboratory tests, and a review of their medical history before being allowed to donate blood or plasma.

All plasma donations are screened for antibody to HIV-1/2 and hepatitis C virus (HCV), and hepatitis B surface antigen (HBsAg). Additional testing of donations is carried out in plasma mini-pools (512 donations per pool) that undergo nucleic acid amplification testing (NAT) for HIV, hepatitis B virus (HBV), HCV, hepatitis A virus (HAV) and parvovirus B19.

Further testing is carried out on the manufacturing pools for HBsAg, and antibody to HIV-1/2; HCV and parvovirus B19 are also tested by NAT, with the limit for B19 set to not exceed 10^4 IU B19 DNA per mL plasma.

There are three processing steps specifically designed to remove or inactivate viruses:

1) Solvent/Detergent treatment is targeted to enveloped viruses;

2) A virus filtration step designed to remove small viruses including non-enveloped viruses, on a size exclusion basis; and

3) The terminal low pH incubation step is identified as contributing to the overall viral clearance capacity for enveloped and non-enveloped viruses.

The capacity of the manufacturing process to remove and/or inactivate enveloped and non-enveloped viruses has been validated by laboratory spiking studies on a scaled down process model. Overall virus reduction was calculated only from steps that were mechanistically independent from each other.

In addition, each step was validated to provide robust virus reduction. Table 5 presents the contribution of each process step to virus reduction and the overall process reduction.

Table 5: Viral Reduction by Process Step
Virus | Type (Envelope/Genome) | Size (nm) | Process Log10 Reduction of Virus (LRV) over manufacturing step
Virus | Type (Envelope/Genome) | Size (nm) | Solvent Detergent | 20 nm filtration | Terminal low pH/elevated temperature incubation | Total LRV
HIV | Env/RNA | 80-100 | >6.8 | I | >6.0 | >12.8
SIN | Env/RNA | 70 | >6.7 | 6.2 | >6.8 | >19.7
WNV | Env/RNA | 50 | >6.4 | I | NT | >6.4
BVDV | Env/RNA | 40-60 | >5.6 | I | >4.6 | >10.2
IBR | Env/DNA | 200 | >5.0 | I | >5.4 | >10.4
HAV | Non-Env/RNA | 30 | NA | >4.8 | 1.3 | >6.1
EMC | Non-Env/RNA | 30 | NA | >4.8 | 3.4 | >8.2
CPV | Non-Env/RNA | 18-24 | NA | 3.2 | 1.0 | 4.2
HIV: Human immunodeficiency virus
SIN: Sindbis virus, model for hepatitis C virus (HCV)
WNV: West Nile Virus
BVDV: Bovine viral diarrhea virus, model for HCV
IBR: Infectious bovine rhinotracheitis, bovine herpes virus model for enveloped DNA viruses including hepatitis B
HAV: Hepatitis A virus
EMC: Encephalomyocarditis, model for HAV
CPV: Canine parvovirus, model for human parvovirus B19
NA: Not applicable, solvent detergent step is limited to the inactivation of enveloped viruses
I: Inactivation by the product intermediate precluded the accurate estimation of the removal of these viruses by the filtration step
NT: Not tested
B19: Viral clearance of human parvovirus B19 was investigated experimentally at the 20 nm filtration step. The estimated Log reduction Factor obtained was 6.0

12 CLINICAL PHARMACOLOGY

12.1 Mechanism of Action

Treatment of Primary Humoral Immunodeficiency

GAMMAPLEX 10% is a replacement therapy for primary humoral immunodeficiency. GAMMAPLEX 10% acts through a broad spectrum of opsonic and neutralizing IgG antibodies against pathogens and their toxins involving antigen binding and effector functions.^13,14 However, the mechanism of action in PI has not been fully elucidated.

Treatment of Chronic Immune Thrombocytopenic Purpura

The mechanism of action of high doses of immunoglobulins in the treatment of chronic ITP has not been fully elucidated.

12.3 Pharmacokinetics

Treatment of Primary Humoral Immunodeficiency

In the cross-over clinical trial assessing bioequivalence, safety and tolerability between GAMMAPLEX 10% and GAMMAPLEX 5% in PI, the pharmacokinetics (PK) of these products was assessed after administration to 30 adult subjects on 28-day (n = 16) or 21-day (n = 14) infusion cycles. Blood samples for PK analysis were obtained after at least five infusions.

The dose of GAMMAPLEX 10% ranged from 361-691 mg/kg for subjects on a 28-day cycle and from 254-794 mg/kg for those on a 21-day cycle. The doses of GAMMAPLEX 5% were similar to those of GAMMAPLEX 10% in this cross-over study. Table 6 compares the other PK variables parameters for GAMMAPLEX 10% and GAMMAPLEX 5% for both the 21-day and 28-day cycle regimens.

GAMMAPLEX 10% was pharmacokinetically equivalent to GAMMAPLEX 5% in adults.

PK outcomes after administration of GAMMAPLEX 10% were assessed in 13 pediatric subjects. Six subjects were on a 28-day regimen and 7 were on a 21-day regimen; doses for the PK assessments ranged from 400 to 745 mg/kg and 355 to 702 mg/kg respectively. Results are shown in Table 6 together with those from the adults in the study.

Table 6: Pharmacokinetic Parameters of GAMMAPLEX 10% compared with GAMMAPLEX 5% in Adults, and GAMMAPLEX 10% in Pediatric Subjects (corrected for baseline concentration)
Indication: | ADULTS |  |  |  | PEDIATRICS
Parameter (unit) | GAMMAPLEX 10% |  | GAMMAPLEX 5% |  | GAMMAPLEX 10%
Parameter (unit) | 28-day Dosing Interval (n=16) | 21-day Dosing Interval (n=14) | 28-day Dosing Interval (n=16) | 21-day Dosing Interval (n=14) | 2-5 years (n=2) | 6-11 years (n=6) | 12-15 years (n=5)
Parameter (unit) | Mean [Geometric mean] (CV%) | Mean (CV%) | Mean (CV%) | Mean (CV%) | Mean (CV%) | Mean (CV%) | Mean (CV%)
Cmax (mg/dL) | 1090 (20.5) | 1150 (27.6) | 1020 (23.6) | 1090 (21.6) | 1120 (33.5) | 907 (37.9) | 977 (34.9)
Tmax (hr) [Median and range are presented for tmax] | 2.87 (1.6-31) | 2.70 (1.8-7.8) | 3.73 (2.1-9.0) | 3.68 (2.2-5.7) | 3.24 (2.8-3.7) | 2.76 (2.0-5.1) | 2.33 (1.7-4.5)
AUC [AUC0-tau = area under the concentration versus time curve within a dosing interval, tau = dosing interval] (days*mg/dL) | 7830 (30.2) | 6980 (33.0) | 7230 (35.3) | 6380 (32.8) | 7620 (70.0) | 6160 (71.1) | 6650 (31.9)
Half-Life (hr) | 123 (32.3) | 118 (39.3) | 132 (45.8) | 119 (48.7) | 167 (9.14) | 111 (37.3) | 144 (16.0)
Clearance (dL/day/kg) | 0.0635 (24.0) | 0.0674 (21.9) | 0.0684 (37.6) | 0.0743 (38.6) | 0.0716 (19.3) | 0.0845 (39.7) | 0.0787 (19.3)
Volume of Distribution (dL/kg) | 0.498 (27.4) | 0.528 (50.3) | 0.569 (38.4) | 0.536 (32.6) | 0.688 (7.45) | 0.571 (28.8) | 0.711 (26.4)
Cmax = maximum observed concentration
Tmax = time at which Cmax was apparent

14 CLINICAL STUDIES

14.1 Treatment of Primary Humoral Immunodeficiency

Pharmacokinetics, Safety and Tolerability study

A cross-over clinical trial assessed bioequivalence, safety and tolerability between GAMMAPLEX 10% and GAMMAPLEX 5% in PI after administration to 33 adult subjects on 28-day (n = 19) or 21-day (n = 14) infusion cycles, of whom 30 (90.9%) completed the PK component [see Pharmacokinetics (12.3)]. Thirty-two subjects completed the study of whom 12 were male and 20 were female. All adults were aged between 17 and 55 years. The mean doses of GAMMAPLEX 10% were 491.7 mg/kg for those on a 28-day cycle and 499.0 mg/kg for those on a 21-day cycle. For GAMMAPLEX 5%, the doses were similar: 473.5 and 502.1 mg/kg respectively. The maximum infusion rate was 0.08 mL/kg/min for each product and this rate was achieved by all adult subjects. In this study, PK bioequivalence was used as a surrogate marker for efficacy. Nevertheless, an ad hoc comparison was made between the products for the number of subjects reporting an infection while on each product. Comparing the number of subjects developing infections of any severity or type while on GAMMAPLEX 10% (22/32) with the period on GAMMAPLEX 5% (17/32) using the McNemar test provided an exact p value of 0.180, confirming the relevance of PK as a surrogate marker. No subject had an acute serious bacterial infection (SABI) during the study.

The pediatric population in the study comprised 15 subjects who received only GAMMAPLEX 10%, of whom 8 were on a 28-day cycle and 7 on a 21-day cycle. Of these, 13 completed the PK component (6 on a 28-day cycle and 7 on a 21-day cycle) [see Pharmacokinetics (12.3)]. There were two subjects in the 2-5 year age group, 7 in the 6-11 year age group and 6 in the 12-15 year age group. The mean dose across all infusions was 535.1 mg/kg. All pediatric subjects tolerated an infusion rate of 0.04 mL/kg/min and 8 subjects (53.3%) tolerated an infusion rate of 0.08 mL/kg/min for all infusions.

Overall, in the population receiving GAMMAPLEX 10%, the PK results (the surrogate for efficacy in this study) and the types and frequencies of adverse reactions were similar for the adult and pediatric populations.

14.2 Treatment of Chronic Immune Thrombocytopenic Purpura

The crossover bioequivalence study described in 14.1, above, did not include subjects with ITP. The results of the bioequivalence study comparing GAMMAPLEX 10% to GAMMAPLEX 5% in subjects with PI are supportive of the potential effectiveness of GAMMAPLEX 10% in the treatment of chronic ITP.

In a Phase 3 multicenter, open-label clinical trial to evaluate the efficacy and safety of GAMMAPLEX 5% in chronic ITP, of the 35 subjects enrolled from various ethnic groups, 9 were male and 26 were female. The age range was between 6 and 69 years. Subjects received intravenous infusions on two consecutive days (1 course) and then observed for a further 30 days. Individuals were given the option of a further two courses of treatment (if required), where only safety variables were assessed. Doses of GAMMAPLEX 5% ranged from 482 to 1149 mg/kg on Day 1 and Day 2. The median total dose per subject was 2035 mg/kg. Subjects received a total of 94 infusions (48 treatment courses).

All 35 subjects received at least one infusion of clinical trial drug, and all but one subject completed the first course of treatment.

The primary analysis was based on the platelet count achieved by Day 9 after the first course of treatment with GAMMAPLEX 5%, response being defined as a platelet count of 50 × 10^9/L or greater. Response to treatment on or before Day 9 was achieved by 29 of 35 subjects (82.9%), and the one-sided 97.5% lower confidence limit of the response rate was 66.4%, which met the a priori success criterion that required it to be greater than 60%.

Efficacy analyses included the duration of response, and changes in the incidences of bleeding or hemorrhage. At Day 32, the median (+ SD) platelet count (24 + [90] × 10^9/L) was still higher than the baseline value, and 11 of 33 subjects (33.3%) continued to show response of platelet counts of 50 × 10^9/L or greater. The median duration of platelet count response for the responders was 10 days.

Table 7: Median Platelet Count (Standard deviation) and Number and Percent of Subjects with a Platelet Count > 50 × 10^9/L during the clinical trial.
Number of days in clinical trial | Day 1 | Day 2 | Day 3 | Day 5 | Day 9 | Day 14 | Day 21 | Day 32
Median Platelet count (× 10^9/L) (Std Dev) | 12.0 (11.4) | 50.0 (36.4) | 93.0 (97.3) | 121.5 (151.9) | 100.5 (201.3) | 15.5 (113.0) | 30.0 (80.0) | 24.0 (89.9)
Number (n/N) and percent of subjects with a platelet count ≥ 50 ×10^9/L | 0/35 (0.0%) | 18/35 (51.4%) | 22/32 (68.8%) | 25/32 (78.1%) | 22/32 (68.8%) | 11/30 (36.7%) | 10/29 (34.5%) | 11/33 (33.3%)
GAMMAPLEX 5% infusions given on Days 1 and 2.

There was an increase in platelet counts for the majority of subjects, and an overall reduction in the manifestations of bleeding after treatment compared to baseline (Day 1). Petechiae, hematomas and gastrointestinal, pulmonary and genitourinary bleeds were all either reduced or absent by Day 32.

There were no thromboembolic episodes reported in the clinical trial; and vital signs, biochemical, hematological and virology tests did not reveal any unexpected pathophysiology or toxicity.

15 REFERENCES

1. Gupta N, Ahmed I, Nissel-Horowitz S, Patel D, Mehrotra B. Intravenous gammaglobulin-associated acute renal failure. Am J Hematol 2001; 66:151-152.
2. Dalakas MC. High-dose intravenous immunoglobulin and serum viscosity: risk of precipitating thromboembolic events. Neurology 1994; 44:223-226.
3. Gabor EP. Meningitis and skin reaction after intravenous immune globulin therapy. Ann Intern Med 1997; 127:1130.
4. Wilson JR, Bhoopalam N, Fisher M. Hemolytic anemia associated with intravenous immunoglobulin. Muscle Nerve 1997; 20:1142-1145.
5. Kessary-Shoham H, Levy Y, Shoenfeld Y, Lorber M, Gershon H. In vivo administration of intravenous immunoglobulin (IVIg) can lead to enhanced erythrocyte sequestration. J Autoimmun 1999; 13:129-135.
6. Kahwaji J, Barker E, Pepkowitz S, et al. Acute Hemolysis After High-Dose Intravenous Immunoglobulin Therapy in Highly HLA Sensitized Patients. Clin J Am Soc Nephrol 2009;4:1993-1997.
7. Daw Z, Padmore R, Neurath D, et al. Hemolytic transfusion reactions after administration of intravenous immune (gamma) globulin: A case series analysis. Transfusion 2008;48:1598-1601.
8. Rizk A, Gorson KC, Kenney L, Weinstein R. Transfusion-related acute lung injury after the infusion of IVIG. Transfusion 2001; 41:264-268.
9. Pierce LR, Jain N. Risks associated with the use of intravenous immunoglobulin. Trans Med Rev 2003; 17:241-251.
10. Siber GA, Werner BG, Halsey NA, Reid R, Almeido-Hill J, Garrett SC, Thompson C, Santosham M. Interference of immune globulin with measles and rubella immunization. J Pediatr 1993; 122:204-211.
11. Salisbury D, Ramsay M, Noakes K, eds. Immunisation against infectious disease. The Stationery Office (TSO), London: UK Department of Health, 2009; p426.
12. Sidiropoulos D, Herrmann U, Morell A, von Muralt G, Barandun S. Transplacental passage of intravenous immunoglobulin in the last trimester of pregnancy. J Pediatr 1986; 109:505-508.
13. Wood P, Stanworth S, Burton J, Jones A, Peckham DG, Chapel H. Recognition, clinical diagnosis and management of patients with primary antibody deficiencies: a systematic review. Clin Exp Immunol 2007; 149:410-423.
14. Simon H, Späth P. IVIG – Mechanisms of action. Allergy 2003; 58(7):543-52.

16 HOW SUPPLIED/STORAGE AND HANDLING

GAMMAPLEX 10% is supplied in a single use, clear Type II glass bottle, closed with a stopper and oversealed with a tamper-evident cap. The components used in the packaging for GAMMAPLEX 10% are not made with natural rubber latex.

The following presentations of GAMMAPLEX 10% are available:

Grams and Fill Size | Carton NDC Number | Vial NDC Number
5 g in 50 mL | 64208-8235-5 | 64208-8235-1
10 g in 100 mL | 64208-8235-6 | 64208-8235-2
20 g in 200 mL | 64208-8235-7 | 64208-8235-3

Each vial has a label with a peel-off strip showing the product name and batch number.

STORAGE AND HANDLING

When stored between 2°C [35.6°F] and 25°C [77°F]), GAMMAPLEX 10% has a shelf life of 36 months.

Keep GAMMAPLEX 10% in its original carton to protect it from light.

Do not shake.

Do not use GAMMAPLEX 10% beyond the expiration date on the product label.

Do not freeze.

17 PATIENT COUNSELING INFORMATION

Inform patients to immediately report the following signs and symptoms to their healthcare professional:

- Decreased urine output, sudden weight gain, fluid retention/edema, and/or shortness of breath [see Warnings and Precautions (5.1)]
- Acute chest pain, shortness of breath, leg pain, and swelling of the legs/feet [see Warnings and Precautions (5.2)]
- Severe headache, neck stiffness, drowsiness, fever, sensitivity to light, painful eye movements, nausea and vomiting [see Warnings and Precautions (5.5)]
- Increased heart rate, fatigue, yellowing of skin or eyes, dark-colored urine [see Warnings and Precautions (5.6)]
- Trouble breathing, chest pain, blue lips or extremities, fever [see Warnings and Precautions (5.7)]

Inform patients that GAMMAPLEX 10% is made from human plasma and may contain infectious agents that can cause disease. While the risk that GAMMAPLEX 10% can transmit an infection has been reduced by screening plasma donors for prior exposure, testing donated plasma, and inactivating or removing certain viruses during manufacturing, patients should report any symptoms that concern them [see Warnings and Precautions (5.9)].

Inform patients that GAMMAPLEX 10% can interfere with their immune response to live viral vaccines (e.g. measles, mumps, and rubella), and instruct patients to notify their healthcare professional of this potential interaction when they are receiving vaccinations [see Drug Interactions (7)].

Instruct patients to immediately report symptoms of thrombosis. These symptoms may include: pain and/or swelling of an arm or leg with warmth over the affected area, discoloration of an arm or leg, unexplained shortness of breath, chest pain or discomfort that worsens on deep breathing, unexplained rapid pulse, numbness or weakness on one side of the body.

Manufactured by:
Bio Products Laboratory Ltd.,
Elstree,
WD6 3BX.
United Kingdom.
U.S. License No. 1811

Marketed by:
Kedrion Biopharma, Inc.,
Parker Plaza,
400 Kelby Street,
Fort Lee, NJ 07024,
United States.

PRINCIPAL DISPLAY PANEL - 50 mL Bottle Label

NDC 64208-8235-1

Immune Globulin Intravenous (Human)
Gammaplex® 10%

5 g

50 mL

solution for infusion

- For intravenous use only
- Directions for use: Read enclosed package
  insert before use. Use immediately after
  piercing cap
- Do not freeze
- Do not use unless clear and free
  from deposit
- Maximum infusion rate 0.08 mL/kg per minute
- Store between 2°C and 25°C (35.6°F and 77°F)
  protected from light

Rx only
GSCUS4L

Marketed by: Kedrion Biopharma, Inc, 400 Kelby St.,
Fort Lee, NJ 07024, United States

Manufactured by: Bio Products Laboratory Ltd.,
Elstree, Borehamwood, WD6 3BX. U.K.

U.S. License No. 1811

PRINCIPAL DISPLAY PANEL - 50 mL Bottle Carton

NDC: 64208-8235-5

Immune Globulin
Intravenous (Human)
Gammaplex® 10%

5 g

solution for infusion

For intravenous use only

Rx only

1 vial

50 mL

Bio Products Laboratory

PRINCIPAL DISPLAY PANEL - 100 mL Bottle Label

NDC 64208-8235-2

Immune Globulin Intravenous (Human)
Gammaplex® 10%

10 g

100 mL

solution for infusion

- For intravenous use only
- Directions for use: Read enclosed package
  insert before use. Use immediately after
  piercing cap
- Do not freeze
- Do not use unless clear and free
  from deposit
- Maximum infusion rate 0.08 mL/kg per minute
- Store between 2°C and 25°C (35.6°F and 77°F)
  protected from light

Rx only
GSAUS4L

Marketed by: Kedrion Biopharma, Inc, 400 Kelby St.,
Fort Lee, NJ 07024, United States

Manufactured by: Bio Products Laboratory Ltd.,
Elstree, Borehamwood, WD6 3BX. U.K.

U.S. License No. 1811

PRINCIPAL DISPLAY PANEL - 100 mL Bottle Carton

NDC: 64208-8235-6

Immune Globulin
Intravenous (Human)
Gammaplex® 10%

10 g

solution for infusion

For intravenous use only

Rx only

1 vial

100 mL

Bio Products Laboratory

PRINCIPAL DISPLAY PANEL - 200 mL Bottle Label

NDC: 64208-8235-3

Immune Globulin Intravenous (Human)
Gammaplex® 10%

20 g

200 mL

solution for infusion

- For intravenous use only
- Directions for use:
  Read enclosed package
  insert before use. Use
  immediately after piercing cap
- Do not freeze
- Do not use unless clear
  and free from deposit
- Maximum infusion rate 0.08 mL/kg
  per minute
- Store between 2°C and 25°C
  (35.6°F and 77°F) protected
  from light

Rx only
GSBUS4L

Marketed by: Kedrion Biopharma, Inc, 400 Kelby St.,
Fort Lee, NJ 07024, United States

Manufactured by: Bio Products Laboratory Ltd.,
Elstree, Borehamwood, WD6 3BX. U.K.

U.S. License No. 1811

PRINCIPAL DISPLAY PANEL - 200 mL Bottle Carton

NDC: 64208-8235-7

Immune Globulin
Intravenous (Human)
Gammaplex® 10%

20 g

solution for infusion

For intravenous use only

Rx only

1 vial

200 mL

Bio Products Laboratory